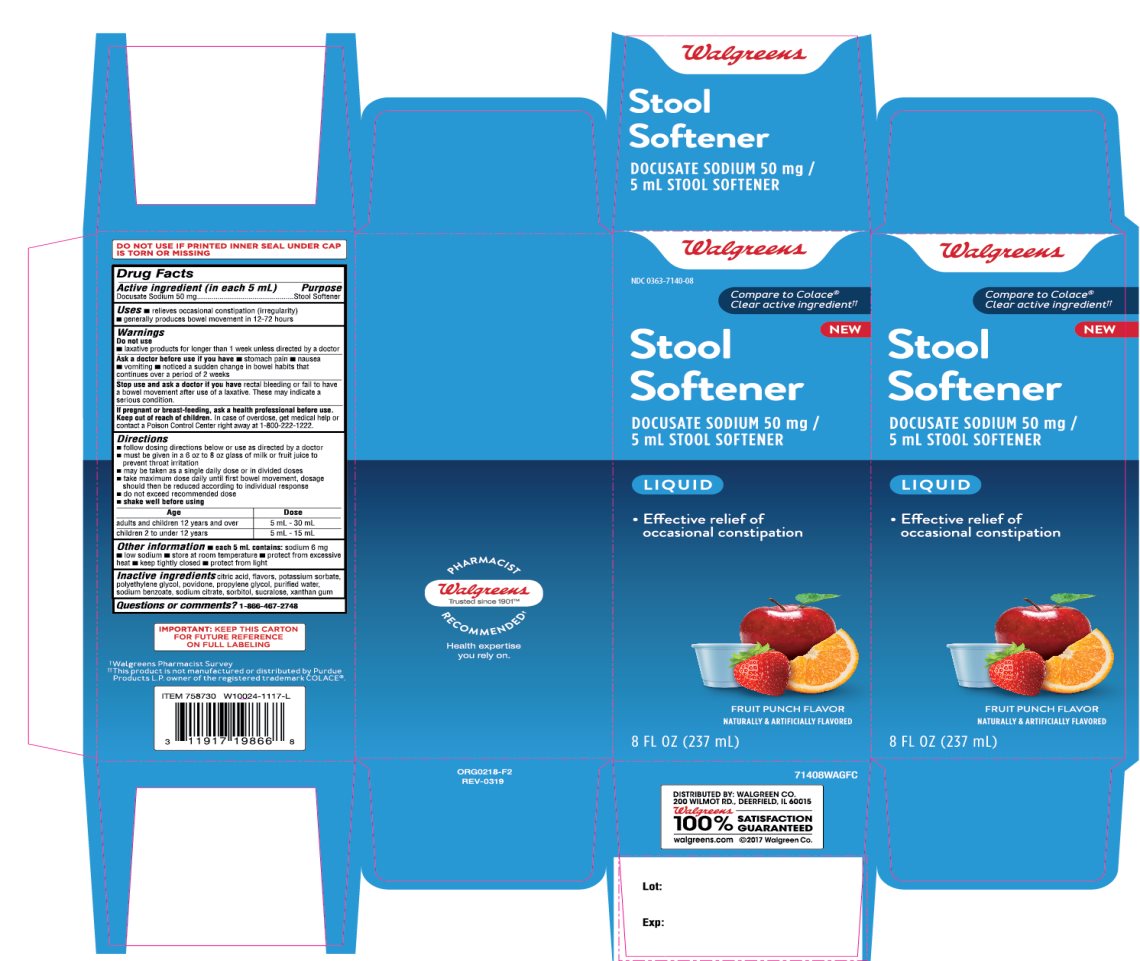 DRUG LABEL: Walgreens Stool Softener

NDC: 0363-7140 | Form: LIQUID
Manufacturer: WALGREENS CO.
Category: otc | Type: HUMAN OTC DRUG LABEL
Date: 20251125

ACTIVE INGREDIENTS: DOCUSATE SODIUM 50 mg/5 mL
INACTIVE INGREDIENTS: ANHYDROUS CITRIC ACID; POTASSIUM SORBATE; POLYETHYLENE GLYCOL, UNSPECIFIED; POVIDONE, UNSPECIFIED; PROPYLENE GLYCOL; WATER; SODIUM BENZOATE; SODIUM CITRATE, UNSPECIFIED FORM; SORBITOL; SUCRALOSE; XANTHAN GUM

Walgreens Stool Softener DOCUSATE LIQUID

Active ingredient (in each 5 mL)

Docusate Sodium 50 mg

Purpose

Stool Softener

Uses

- relieves occasional constipation (irregularity)
- generally produces bowel movement in 12 to 72 hours

Warnings

Do not use

- laxative products for longer than 1 week unless directed by a doctor

Ask a doctor before use if you have

- stomach pain
- nausea
- vomiting
- noticed a sudden change in bowel habits that continues over a period of 2 weeks

Stop use and ask a doctor if you haverectal bleeding of fail to have a bowel movement after use of laxative. These may indicate a serious condition.

PREGNANCY OR BREAST FEEDING

If pregnant or breast feeding, ask a health professional before use.

Keep out of reach of children. In case of overdose, get medical help or contact a poison control Center right away at 1-800-222-1222.

Directions

- follow dosing directions below or take as directed by doctor
- must be given in a 6 to 8 oz glass of milk or fruit juice to prevent throat irritation
- may be taken as a single daily dose or in divided doses
- take maximum dose daily until first bowel movement, dosage should then be reduced according to individual response.
- do not exceed recommended dose
- shake well before using

Age | Dose
Adults and children 12 years and over | 5 mL-30 mL
Children 2 to under 12 years | 5 mL-15 mL

Other information

- each 5 mL contains:sodium 6 mg
- low sodium
- store at room temperature
- protect from excessive heat
- keep tightly closed
- protect from light

SAFETY SEALED: DO NOT USE IF PRINTED INNER SEAL UNDER CAP IS TORN OR MISSING

Inactive ingredients

citric acid, flavor, potassium sorbate, polyethylene glycol, povidone, propylene glycol, purified water, sodium benzoate, sodium citrate, sorbitol, sucralose, xanthan gum.

Questions or comments?

1-866-467-2748

Principal Display Panel

NDC 0363-7140-08

Compare to Colace® Clear active ingredient††

Walgreens

Stool Softener
DOCUSATE SODIUM 50 MG/5 ML STOOL SOFTENER

LIQUID

Effective relief of occasional constipation

FRUIT PUNCH FLAVOR

NATURALLY AND ARTIFICIALLY FLAVOR
8 FL OZ (237 mL)

Package Contains One Bottle

DISTRIBUTED BY: WALGREEN CO.

200 WILMOT RD., DEERFIELD, IL 60015

Walgreens 100 % SATISFACTION GUARANTEED

Walgreens.com © 2017 walgreen.com

†Walgreens Pharmacist Survey

*This product is not manufactured or distributed by Purdue Products L.P., owner of the registered trademark COLACE®.

IMPORTANT: Keep this carton for future reference on full labeling.